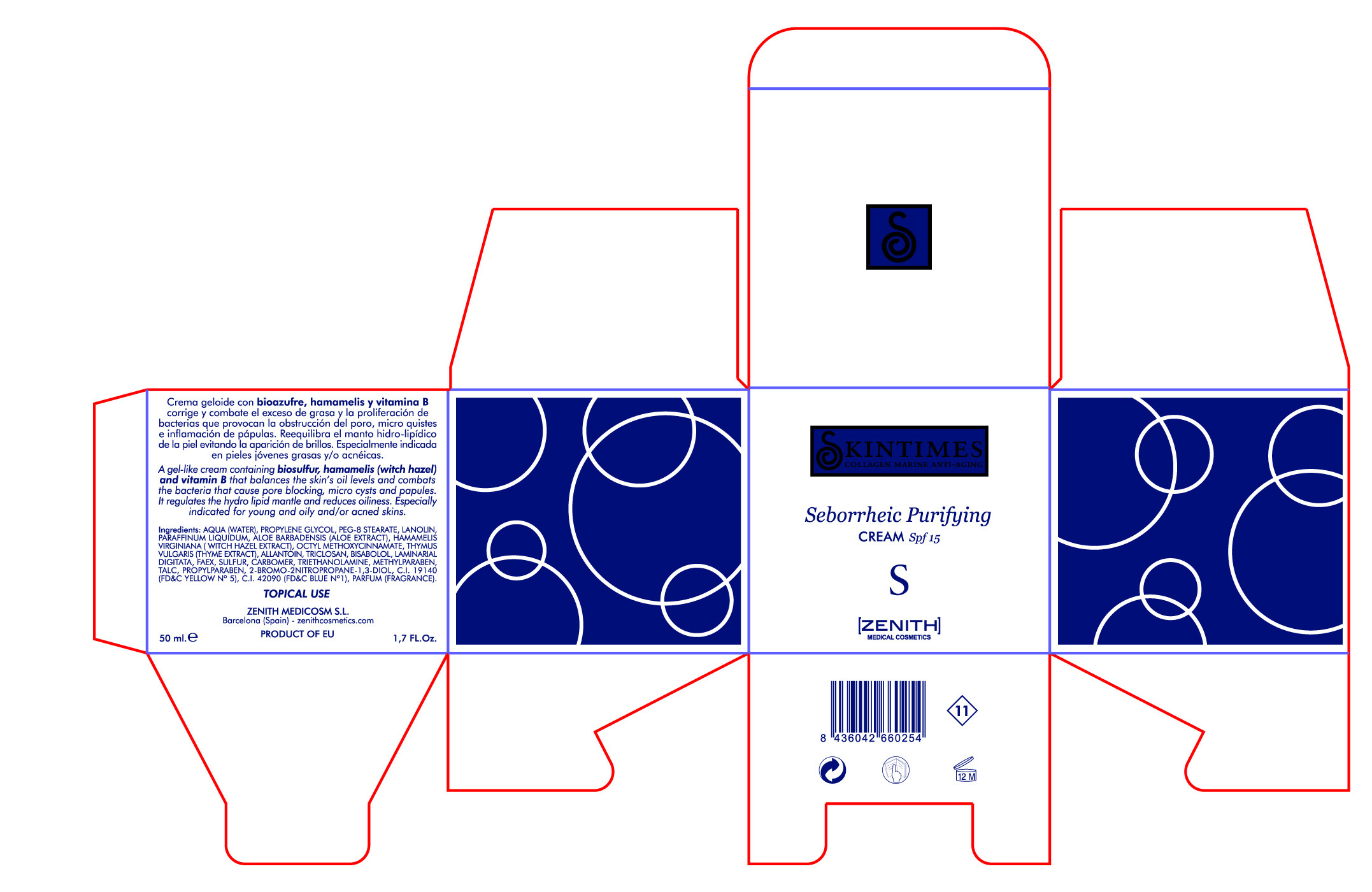 DRUG LABEL: Seborrheic
NDC: 42248-108 | Form: CREAM
Manufacturer: Zenith Medicosm SL
Category: otc | Type: HUMAN OTC DRUG LABEL
Date: 20120121

ACTIVE INGREDIENTS: OCTINOXATE 3.75 mL/50 mL
INACTIVE INGREDIENTS: LANOLIN; PROPYLPARABEN; TALC; THYME; ALOE; HAMAMELIS VIRGINIANA LEAF; WATER; MINERAL OIL; TRICLOSAN; PEG-8 STEARATE; TROLAMINE; LEVOMENOL; SULFUR; YEAST; LAMINARIA DIGITATA; CARBOMER 934; ALLANTOIN; PROPYLENE GLYCOL; METHYLPARABEN; COLLAGEN, SOLUBLE, FISH SKIN; FD&C BLUE NO. 1; FD&C YELLOW NO. 5

Drug Facts

Active Ingredient

Octinoxate 7.5%

Description

A gel-like cream containing biosulfur, hamamelis (witch hazel) and vitamin B that balances the skin's oil levels and combats the bacteria that cause pore blocking, micro cysts and papules. It regulates the hydro lipid mantle and reduces oiliness. Especially indicated for young and oily and/or acned skins.

50ml. 1.7 fl. Oz

Warning

TOPICAL USE